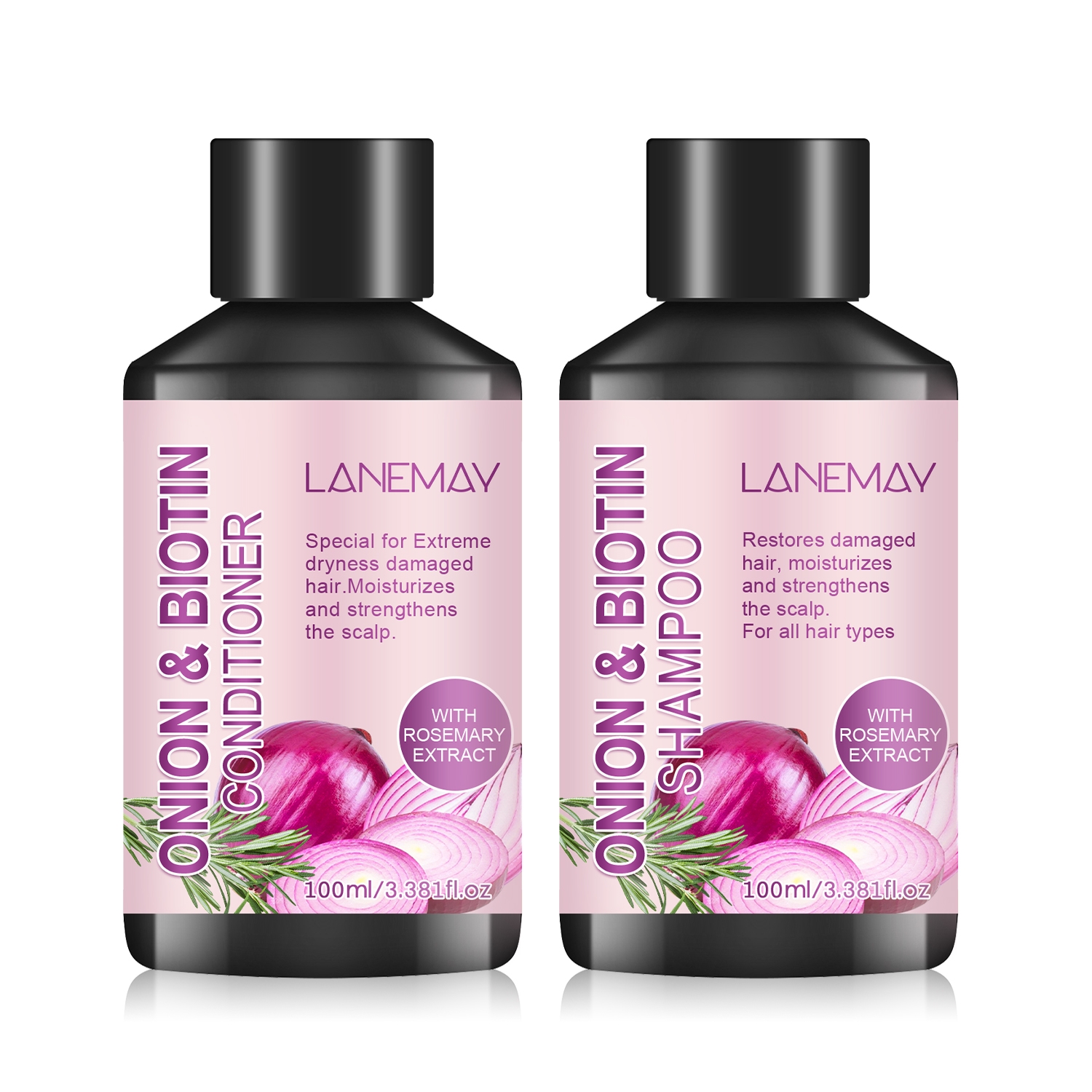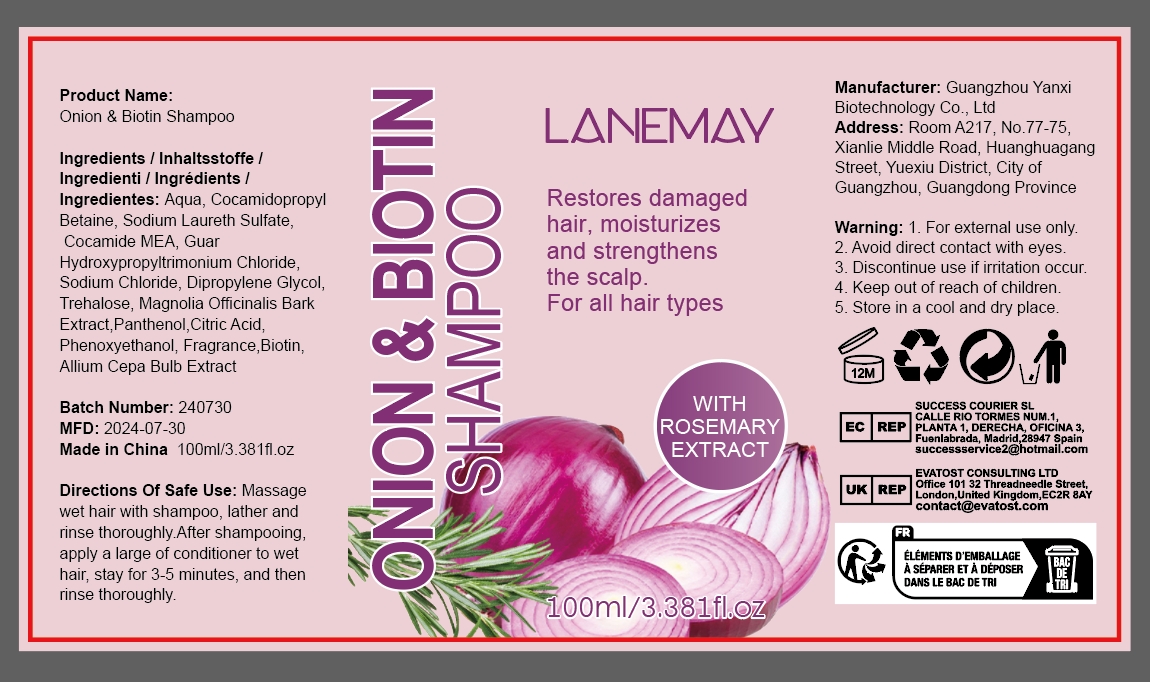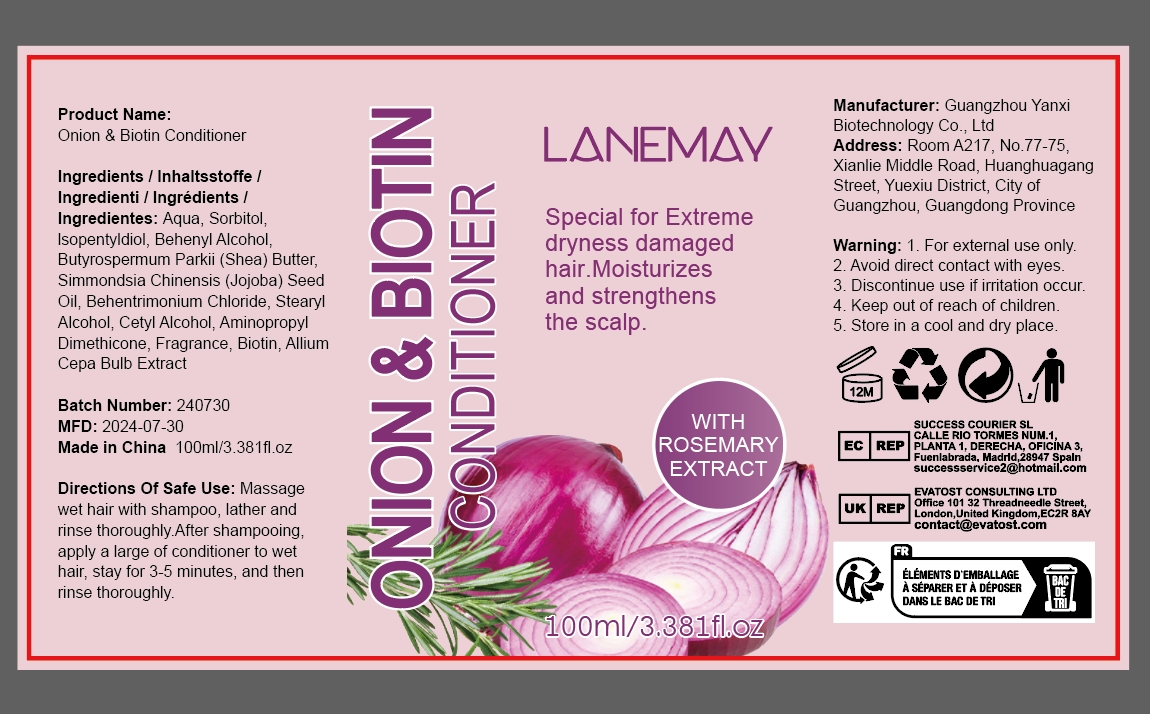 DRUG LABEL: Onion BiotinShampoo And Conditioner Set
NDC: 84025-148 | Form: SHAMPOO
Manufacturer: Guangzhou Yanxi Biotechnology Co.. Ltd
Category: otc | Type: HUMAN OTC DRUG LABEL
Date: 20240815

ACTIVE INGREDIENTS: DIPROPYLENE GLYCOL 3 mg/100 mL; COCAMIDOPROPYL BETAINE 5 mg/100 mL
INACTIVE INGREDIENTS: WATER

DOSAGE AND ADMINISTRATION

For moisturizing hair and repairing damaged hair

WARNINGS

Keep out of children

INACTIVE INGREDIENT

Aqua

INDICATIONS AND USAGE

For daily hair and scalp care

Keep out of children

PURPOSE

Effectively relieve dry hair and keep scalp healthy